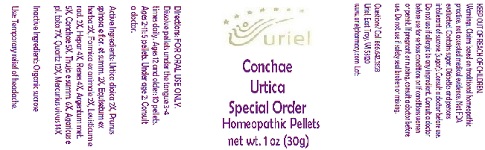 DRUG LABEL: Conchae Urtica Special Order
NDC: 48951-3119 | Form: PELLET
Manufacturer: Uriel Pharmacy Inc.
Category: homeopathic | Type: HUMAN OTC DRUG LABEL
Date: 20180604

ACTIVE INGREDIENTS: URTICA DIOICA ROOT 2 [hp_X]/1 1; SLOE 2 [hp_X]/1 1; EQUISETUM ARVENSE TOP 2 [hp_X]/1 1; FORMICA RUFA 2 [hp_X]/1 1; LEVISTICUM OFFICINALE ROOT 2 [hp_X]/1 1; MAMMAL LIVER 4 [hp_X]/1 1; PORK KIDNEY 4 [hp_X]/1 1; SILVER 5 [hp_X]/1 1; OSTREA EDULIS SHELL 5 [hp_X]/1 1; THUJA OCCIDENTALIS WHOLE 6 [hp_X]/1 1; AMANITA MUSCARIA FRUITING BODY 7 [hp_X]/1 1; SILICON DIOXIDE 12 [hp_X]/1 1; MERCURY 14 [hp_X]/1 1
INACTIVE INGREDIENTS: SUCROSE

Conchae Urtica Special Order

INDICATIONS AND USAGE

Directions: FOR ORAL USE ONLY.

DOSAGE AND ADMINISTRATION

Dissolve pellets under the tongue 3-4 times daily. Ages 12 and older: 10 pellets. Ages 2-11: 5 pellets. Under age 2: Consult a doctor.

ACTIVE INGREDIENT

Active Ingredients: Urtica dioica 2X, Prunus spinosa e flor. et summ. 2X, Equisetum ex herba 2X, Formica ex animale 2X, Levisticum e rad. 2X, Hepar 4X, Renes 4X, Argentum met. 5X, Conchae 5X, Thuja e summ. 6X, Agaricus e pl. tota 7X, Quartz 12X, Mercurius vivus 14X

Inactive Ingredient: Organic sucrose

PURPOSE

Use: Temporary relief of headache.

KEEP OUT OF REACH OF CHILDREN.

WARNINGS

Warnings: Claims based on traditional homeopathic practice, not accepted medical evidence. Not FDA evaluated. Contains sugar. Diabetics and persons intolerant of sucrose (sugar): Consult a doctor before use. Do not use if allergic to any ingredient. Consult a doctor before use for serious conditions or if conditions worsen or persist. If pregnant or nursing, consult a doctor before use. Do not use if safety seal broken or missing.

QUESTIONS

Questions? Call 866.642.2858 Uriel, East Troy, WI 53120 www.urielpharmacy.com